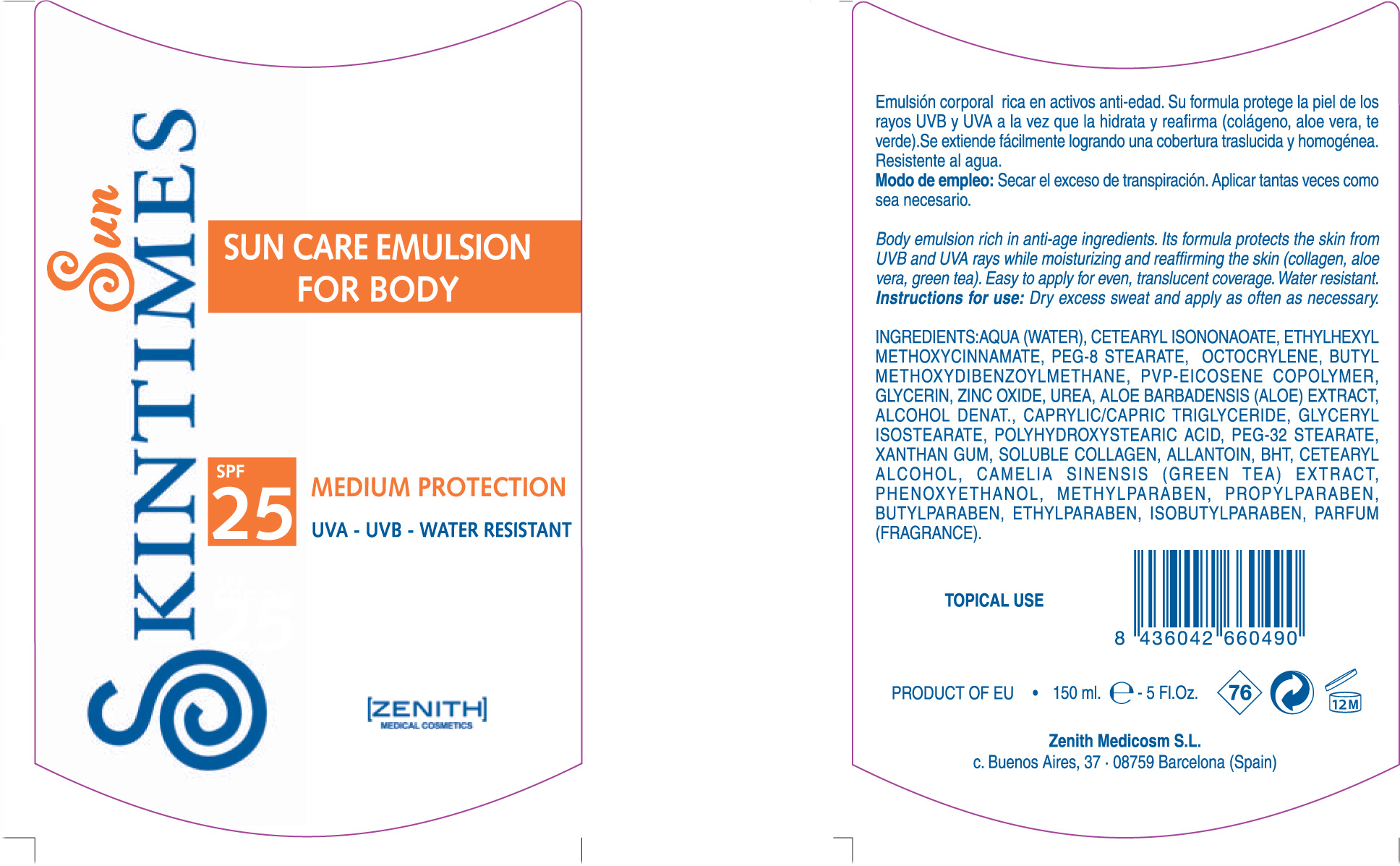 DRUG LABEL: SUN CARE
NDC: 42248-122 | Form: EMULSION
Manufacturer: Zenith Medicosm SL
Category: otc | Type: HUMAN OTC DRUG LABEL
Date: 20120121

ACTIVE INGREDIENTS: OCTINOXATE 11.25 mL/150 mL; AVOBENZONE  4.5 mL/150 mL; ZINC OXIDE 36 mL/150 mL; OCTOCRYLENE 15 mL/150 mL
INACTIVE INGREDIENTS: ALOE VERA LEAF; PROPYLPARABEN; METHYLPARABEN; COLLAGEN, SOLUBLE, FISH SKIN; PEG-8 STEARATE; POLYQUATERNIUM-7 (70/30 ACRYLAMIDE/DADMAC; 900 KD); WATER; TRICAPRYLIN; GLYCERYL ISOSTEARATE; POLYHYDROXYSTEARIC ACID (2300 MW); C12-14 ISOPARAFFIN; 1-ETHYL-2-PYRROLECARBOXALDEHYDE; RICE GERM; GREEN TEA LEAF; CETEARYL ISONONANOATE; LAURETH-7; XANTHAN GUM; GLYCERIN; METHYLPARABEN; ISOBUTYLPARABEN; ALLANTOIN; PHENOXYETHANOL; BUTYLPARABEN; ETHYLPARABEN; CETOSTEARYL ALCOHOL; ALCOHOL; PEG-32 STEARATE

Drug Facts

Active Ingredient

Octinoxate 7.5%

Octocrylene 10%

Avobenzone 3%

Zinc Oxide 24%

Description

SUN CARE CREAM FOR BODY

SPF 25

MEDIUM PROTECTION

UVA - UVB - WATER RESISTANT

Body emulsion rich in anti-age ingredients. Its formula protects skin from UVB and UVA rays while moisturizing and reaffirming the skin (collagen, aloe vera, green tea). Easy o apply for even, translucent coverage. Water resistant.

150ml. 5Fl.Oz.

Warning

TOPICAL USE

Instructions for use

Dry excess sweat and apply as often as necessary.